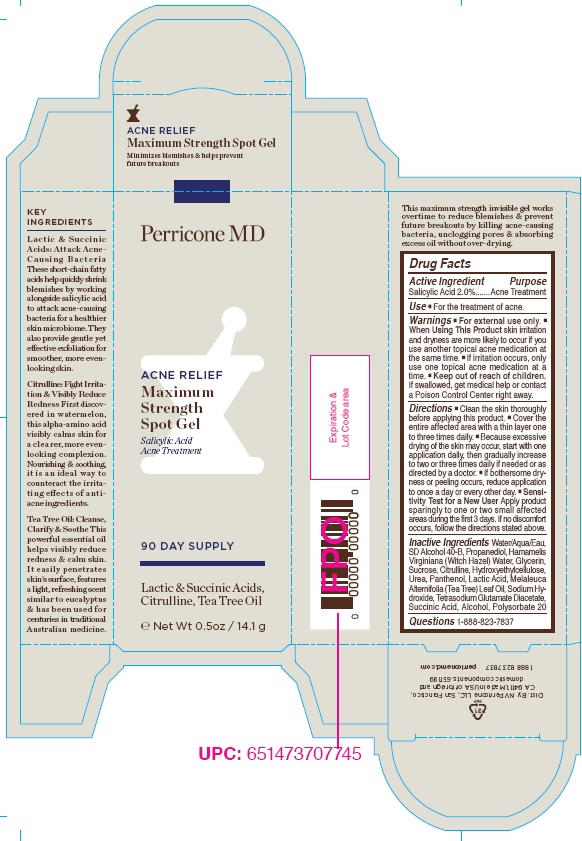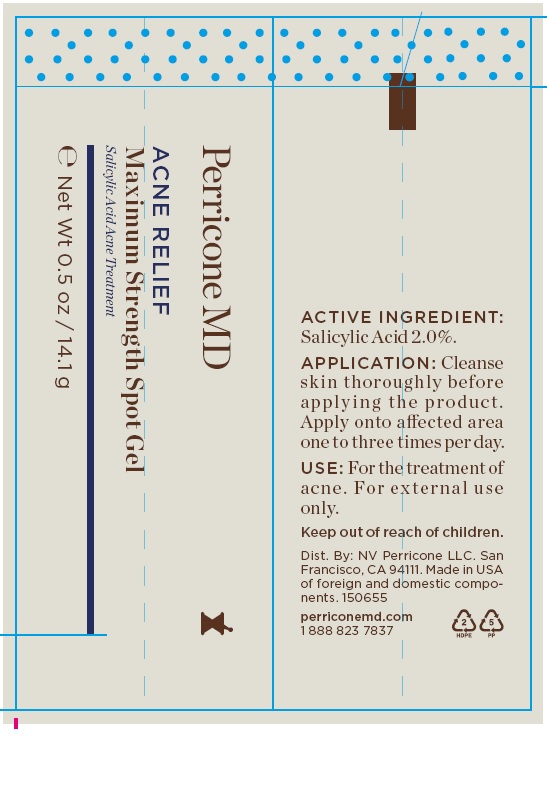 DRUG LABEL: Acne Relief Maximum Strength Spot Gel
NDC: 45634-100 | Form: GEL
Manufacturer: NV Perricone LLC
Category: otc | Type: HUMAN OTC DRUG LABEL
Date: 20220210

ACTIVE INGREDIENTS: SALICYLIC ACID 2 g/100 g
INACTIVE INGREDIENTS: WATER; ALCOHOL; PROPANEDIOL; HAMAMELIS VIRGINIANA TOP WATER; GLYCERIN; SUCROSE; CITRULLINE; HYDROXYETHYL CELLULOSE (100 MPA.S AT 2%); UREA; PANTHENOL; LACTIC ACID; TEA TREE OIL; SODIUM HYDROXIDE; TETRASODIUM GLUTAMATE DIACETATE; SUCCINIC ACID; POLYSORBATE 20

ACNE RELIEF MAXIMUM STRENGTH SPOT GEL

Drug Facts

Active Ingredient
Salicylic Acid 2.0%

Purpose
Acne Treatment

INDICATIONS AND USAGE

Use■ For the treatment of acne.

Warnings■ For external use only. ■
When Using This Product skin irritation
and dryness are more likely to occur if you
use another topical acne medication at
the same time. ■ If irritation occurs, only
use one topical acne medication at a
time. ■ Keep out of reach of children.
If swallowed, get medical help or contact
a Poison Control Center right away.

DOSAGE AND ADMINISTRATION

Directions ■ Clean the skin thoroughly
before applying this product. ■ Cover the
entire affected area with a thin layer one
to three times daily. ■ Because excessive
drying of the skin may occur, start with one
application daily, then gradually increase
to two or three times daily if needed or as
directed by a doctor. ■ If bothersome dryness
or peeling occurs, reduce application
to once a day or every other day. ■ Sensitivity
Test for a New User Apply product
sparingly to one or two small affected
areas during the first 3 days. If no discomfort
occurs, follow the directions stated above.

Inactive Ingredients Water/Aqua/Eau,
SD Alcohol 40-B, Propanediol, Hamamelis
Virginiana (Witch Hazel) Water, Glycerin,
Sucrose, Citrulline, Hydroxyethylcellulose,
Urea, Panthenol, Lactic Acid, Melaleuca
Alternifolia (Tea Tree) Leaf Oil, Sodium Hydroxide,
Tetrasodium Glutamate Diacetate,
Succinic Acid, Alcohol, Polysorbate 20

QUESTIONS

Questions1-888-823-7837

Product Package

ACNE RELIEF
Maximum Strength Spot Gel
Minimizes blemishes & helps prevent
future breakouts

Perricone MD

ACNE RELIEF

Maximum
Strength
Spot Gel

Salicylic Acid
Acne Treatment

90 DAY SUPPLY

Lactic & Succinic Acids,
Citrulline, Tea Tree Oil

℮ Net Wt 0.5oz / 14.1 g

KEY
INGREDIENTS

Lactic & Succinic
Acids: Attack Acne-
Causing Bacteria
These short-chain fatty
acids help quickly shrink
blemishes by working
alongside salicylic acid
to attack acne-causing
bacteria for a healthier
skin microbiome. They
also provide gentle yet
effective exfoliation for
smoother, more even-looking
skin.

Citrulline: Fight Irritation
& Visibly Reduce
Redness First discovered
in watermelon,
this alpha-amino acid
visibly calms skin for
a clearer, more even-looking
complexion.
Nourishing & soothing,
it is an ideal way to
counteract the irritating
effects of antiacne
ingredients.

Tea Tree Oil: Cleanse,
Clarify & Soothe This
powerful essential oil
helps visibly reduce
redness & calm skin.
It easily penetrates
skin’s surface, features
a light, refreshing scent
similar to eucalyptus
& has been used for
centuries in traditional
Australian medicine.

This maximum strength invisible gel works
overtime to reduce blemishes & prevent
future breakouts by killing acne-causing
bacteria, unclogging pores & absorbing
excess oil without over-drying.

Dist. By: NV Perricone LLC, San Francisco,
CA 94111. Made in USA of foreign and
domestic components. 651199

1 888 823 7837 perriconemd.com

Expiration &
Lot Code area

Outer Box

Tube

rege